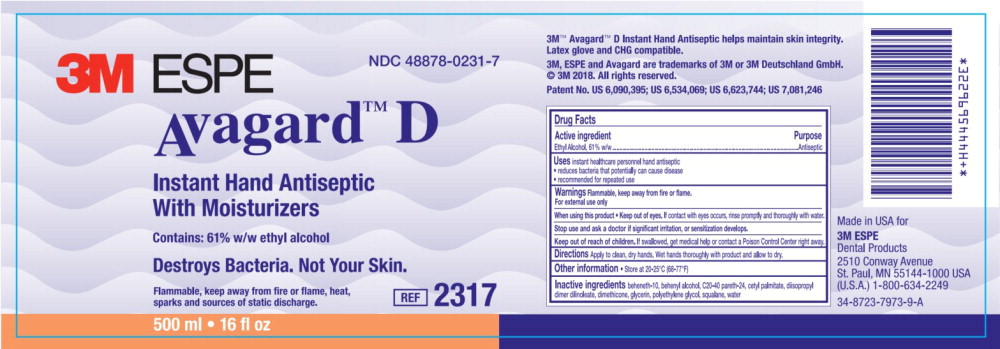 DRUG LABEL: Avagard D
NDC: 48878-0231 | Form: LOTION
Manufacturer: Solventum US LLC
Category: otc | Type: HUMAN OTC DRUG LABEL
Date: 20260108

ACTIVE INGREDIENTS: Alcohol 530.7 mg/1 mL
INACTIVE INGREDIENTS: Beheneth-10; Docosanol; Cetyl Palmitate; Dimethicone; Glycerin; Polyethylene Glycol, unspecified; Squalane; Water

Drug Facts

Active Ingredient

Ethyl Alcohol, 61% w/w

Purpose

Antiseptic

Uses

instant healthcare personnel hand antiseptic

- reduces bacteria that potentially can cause disease
- recommended for repeated use

Warnings

Flammable, keep away from fire or flame.

For external use only

When using this product

- Keep out of eyes. If contact with eyes occurs, rinse promptly and thoroughly with water.

Stop use and ask a doctor if significant irritation, or sensitization develops.

Keep out of reach of children. If swallowed, get medical help or contact a Poison Control Center right away.

Directions

Apply to clean, dry hands. Wet hands thoroughly with product and allow to dry.

Other information

- Store at 20-25°C (68-77°F)

Inactive ingredient

beheneth-10, behenyl alcohol, C20-40 pareth-24, cetyl palmitate, diisopropyl dimer dilinoleate, dimethicone, glycerin, polyethylene glycol, squalane, water

Principal Display Panel

NDC 48878-0231-7

3M ESPE

Avagard™ D

Instant Hand Antiseptic

With Moisturizers

Contains: 61% w/w ethyl alcohol

Destroys Bacteria. Not Your Skin.

Flammable, keep away from fire or flame, heat,

sparks and sources of static discharge.

REF 2317

500 ml • 16fl oz